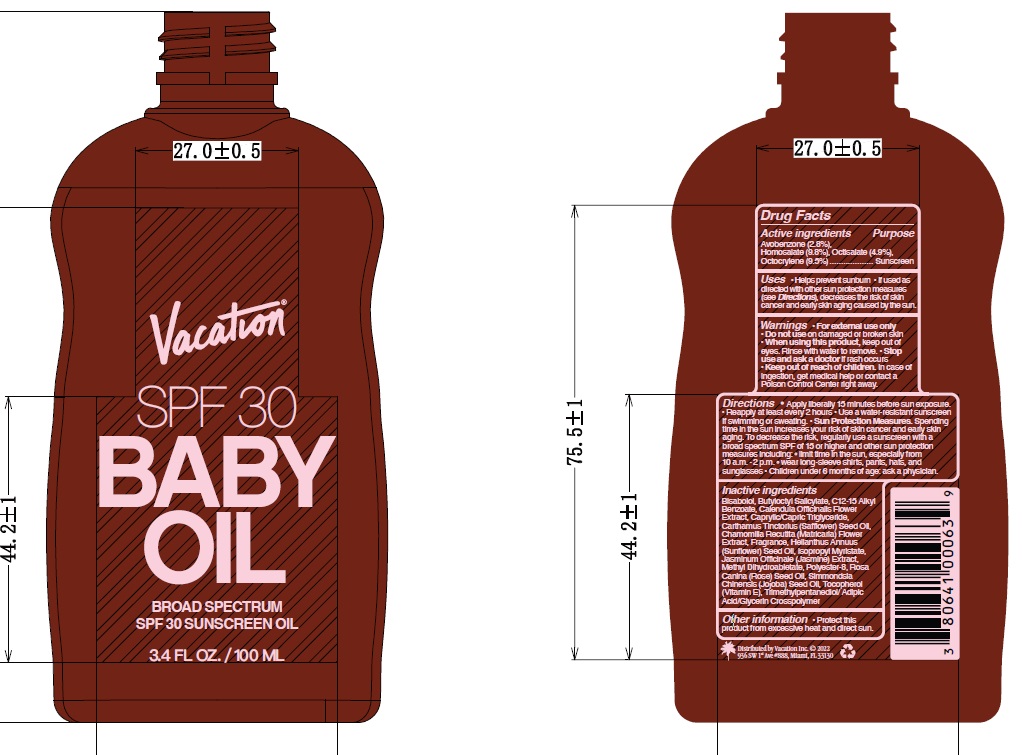 DRUG LABEL: Vacation SPF 30 Baby Oil
NDC: 80641-011 | Form: OIL
Manufacturer: Vacation Inc.
Category: otc | Type: HUMAN OTC DRUG LABEL
Date: 20240306

ACTIVE INGREDIENTS: HOMOSALATE 9.8 g/100 mL; OCTISALATE 4.9 g/100 mL; AVOBENZONE 2.8 g/100 mL; OCTOCRYLENE 9.5 g/100 mL
INACTIVE INGREDIENTS: LEVOMENOL; BUTYLOCTYL SALICYLATE; ALKYL (C12-15) BENZOATE; CALENDULA OFFICINALIS FLOWER; TRIMETHYLPENTANEDIOL/ADIPIC ACID/GLYCERIN CROSSPOLYMER (25000 MPA.S); MATRICARIA RECUTITA FLOWERING TOP; SUNFLOWER OIL; JASMINUM OFFICINALE FLOWER; MEDIUM-CHAIN TRIGLYCERIDES; METHYL DIHYDROABIETATE; POLYESTER-8 (1400 MW, CYANODIPHENYLPROPENOYL CAPPED); ROSA CANINA SEED OIL; JOJOBA OIL; TOCOPHEROL; SAFFLOWER OIL; ISOPROPYL MYRISTATE

Vacation - SPF 30 Baby Oil

ACTIVE INGREDIENT

Avobenzone (2.8%)

Homosalate (9.8%)

Octisalate (4.9%)

Octocrylene (9.5%)

PURPOSE

Sunscreen

Uses

• Helps prevent sunburn

• If used as directed with other sun protection measures (see Directions), decreases the risk of skin cancer and early skin aging caused by the sun.

Warnings

• For external use only
• Do not use on damaged or broken skin
• When using this product, keep out of eyes. Rinse with water to remove.

• Stop use and ask a doctor if rash occurs

• Keep out of reach of children. In case of ingestion, get medical help or contact a Poison Control Center right away.

Directions

• Apply liberally 15 minutes before sun exposure.
• Reapply at least every 2 hours

• Use a water-resistant sunscreen if swimming or sweating.

• Sun Protection Measures. Spending time in the sun increases your risk of skin cancer and early skin aging. To decrease the risk, regularly use a sunscreen with a broad spectrum SPF of 15 or higher and other sun protection measures including: limit time in the sun, especially from 10 a.m. - 2 p.m. wear long-sleeve shirts, pants, hats, and sunglasses • Children under 6 months of age: ask a physician.

INACTIVE INGREDIENT

Bisabolol, Butyloctyl Salicylate, C12-15 Alkyl Benzoate, Calendula Officinalis Flower Extract, Caprylic/Capric Triglyceride, Carthamus Tinctorius (Safflower) Seed Oil, Chamomilla Recutita (Matricaria) Flower Extract, Fragrance, Helianthus Annuus (Sunflower) Seed Oil, Isopropyl Myristate, Jasminum Officinale (Jasmine) Extract, Methyl Dihydroabietate, Polyester-8, Rosa Canina (Rose) Seed Oil, Simmondsia Chinensis (Jojoba) Seed Oil, Tocopherol (Vitamin E), Trimethylpentanediol/ Adipic Acid/Glycerin Crosspolymer

Other Information

• Protect this product from excessive heat and direct sun.